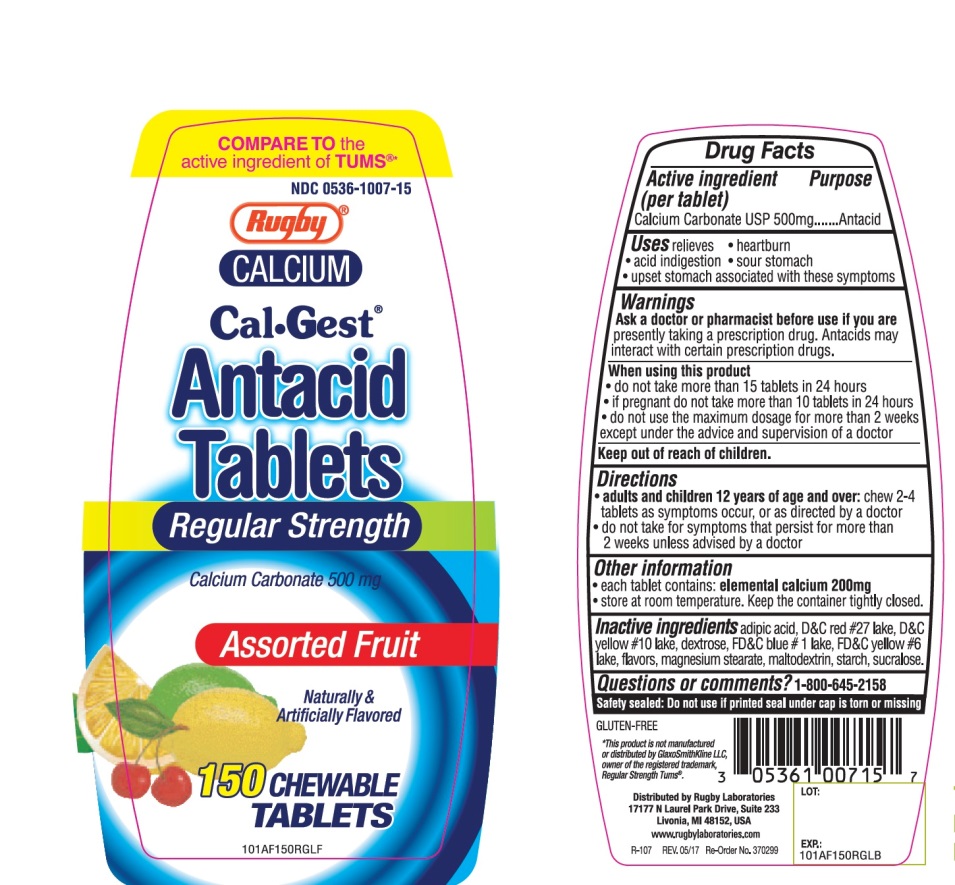 DRUG LABEL: Rugby Cal-Gest Antacid

NDC: 0536-1007 | Form: TABLET, CHEWABLE
Manufacturer: Rugby Laboratories, Inc.
Category: otc | Type: HUMAN OTC DRUG LABEL
Date: 20251025

ACTIVE INGREDIENTS: CALCIUM CARBONATE 500 mg/1 1
INACTIVE INGREDIENTS: ADIPIC ACID; D&C RED NO. 27; D&C YELLOW NO. 10; DEXTROSE, UNSPECIFIED FORM; FD&C BLUE NO. 1; FD&C YELLOW NO. 6; MAGNESIUM STEARATE; MALTODEXTRIN; STARCH, CORN; SUCRALOSE

Rugby Assorted Flavors Cal-Gest Antacid 150 Chewable Tablets

Active ingredient (per tablet)

Calcium Carbonate USP 500mg

Purpose

Antacid

Uses

relieves:

- heartburn
- sour stomach
- acid indigestion
- upset stomach associated with these symptoms

Warnings

Ask a doctor or pharmacist before use if you aretaking a prescription drug. Antacids may interact with certain prescription drugs.

When using this product

- do not take more than 15 tablets in 24 hours
- if pregnant do not take more than 10 tablets in 24 hours.
- do not use the maximum dosage for more than 2 weeks except under advice and supervision of a doctor

Directions

- adults and children 12 years of age and over:chew 2-4 tablets as symptoms occur, or as directed by a doctor.
- do not take for symptoms that persist for more than 2 weeks unless advised by a doctor

Other Information

- each tablet contains: elemental calcium 200 mg
- Store at room temperature. Keep the container tightly closed

Inactive ingredients

adipic acid, D&C red#27 lake, D&C yellow# 10 lake, dextrose, FD&C blue #1 lake, FD&C yellow #6 lake, flavors, magnesium stearate, maltodextrin, starch, sucralose.

Questions or comments?

1-800-645-2158

Package/Label Principal Display Panel

COMPARE TO active ingredient in TUMS®*

NDC# 0536-1007-15

Rugby®

CALCIUM

Cal-Gest®

Antacid Tablets

Regular Strength

Calcium Carbonate 500 mg

Assorted Fruit

Naturally & Artificially Flavored

150 CHEWABLE TABLETS

Safety sealed: Do not use if printed seal under cap is torn or missing

GLUTEN-FREE

*This product is not manufactured or distributed by GlaxoSmithKline LLC, owner of the registered trademark, Regular Strength Tums®

Distributed by Rugby Laboratories

17177 N Laurel Park Drive, Suite 233

Livonia, MI 48152, USA

www.rugbylaboratories.com